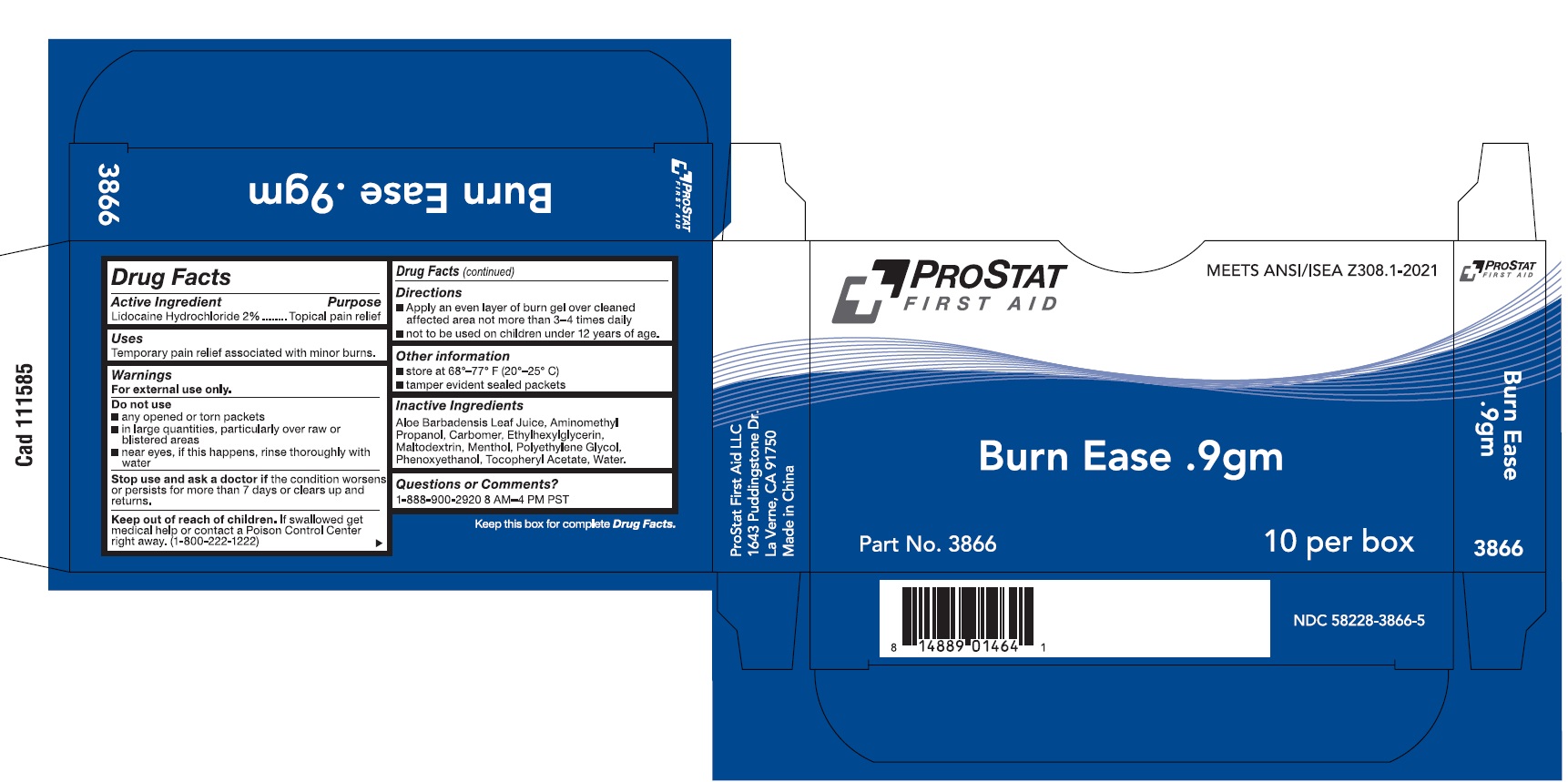 DRUG LABEL: PROSTAT FIRST AID Burn Ease, 0.9g
NDC: 58228-3867 | Form: GEL
Manufacturer: ProStat First Aid LLC
Category: otc | Type: HUMAN OTC DRUG LABEL
Date: 20251001

ACTIVE INGREDIENTS: LIDOCAINE HYDROCHLORIDE 2 g/100 g
INACTIVE INGREDIENTS: CARBOMER HOMOPOLYMER TYPE C (ALLYL PENTAERYTHRITOL CROSSLINKED); AMINOMETHYL PROPANOL; ETHYLHEXYLGLYCERIN; MALTODEXTRIN; PROPYLENE GLYCOL; MENTHOL; PHENOXYETHANOL; WATER; .ALPHA.-TOCOPHEROL ACETATE; ALOE BARBADENSIS LEAF JUICE

58228-3867-1 PS-3866 Burn Ease 0.9g

Active Ingredient

Lidocaine Hydrochloride 2%

Purpose

Topical Pain Relief

Use(s)

Temporary pain relief associated with minor burns

Warnings

For External Use Only

Do not use

• any opened or torn packets

• in large quantities, particularly over raw or blistered areas

- Near eyes. If this happens, rinse thoroughly with water

WHEN USING

• Avoid contact with the eyes

• Do not bandage tightly

Stop use and ask a doctor if

• Condition worsens or persists for more than 7 days or clears up and returns

Keep out of reach of children

If swallowed, get medical help or contact a Poison Control Center (1-800-222-1222) right away.

Directions

Apply an even layer of burn gel over cleaned affected area not more than 3-4 times daily

Not to be used on children under 12 years of age

Other Information

• store at 68-77F (20-25C)

- tamper evident sealed packets

Inactive Ingredients

Aloe Barbadensis Leaf Juice, Aminomethyl propanol, Carbomer, Ethylhexylglycerin, Maltodextrin, Menthol, Polyethylene glycol, Phenoxyethanol, Tocopheryl Acetate, Water

Questions?

1-888-900-2920 8AM - 4PM PST